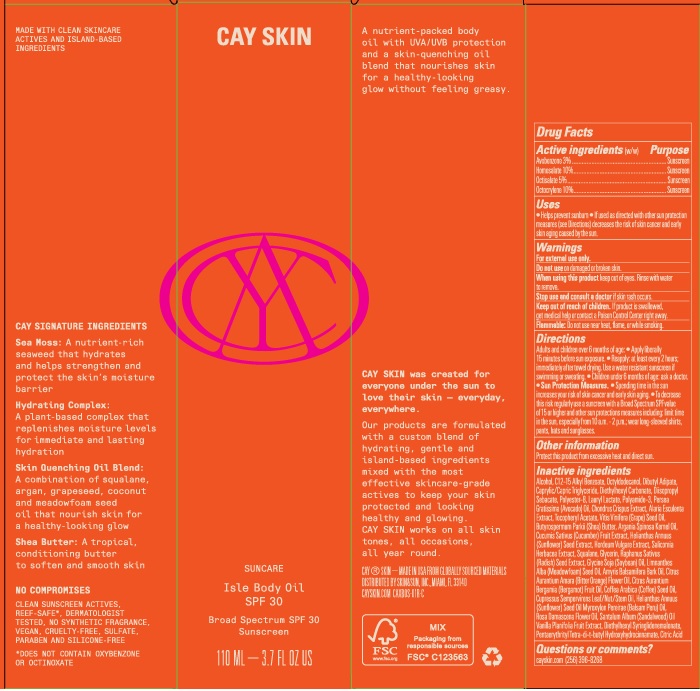 DRUG LABEL: Cay Skin Isle Body Oil SPF 30
NDC: 82657-006 | Form: OIL
Manufacturer: Cay Skin, Inc.
Category: otc | Type: HUMAN OTC DRUG LABEL
Date: 20241205

ACTIVE INGREDIENTS: AVOBENZONE 30 mg/1 mL; OCTISALATE 50 mg/1 mL; OCTOCRYLENE 100 mg/1 mL; HOMOSALATE 100 mg/1 mL
INACTIVE INGREDIENTS: SHEA BUTTER; ARGAN OIL; MEADOWFOAM SEED OIL; SQUALANE; SOYBEAN OIL; CITRUS AURANTIUM FLOWER OIL; SUNFLOWER SEED; DIETHYLHEXYL CARBONATE; DIISOPROPYL SEBACATE; .ALPHA.-TOCOPHEROL ACETATE; CUPRESSUS SEMPERVIRENS WHOLE; SUNFLOWER OIL; ROSA DAMASCENA FLOWER OIL; ALKYL (C12-15) BENZOATE; VANILLA BEAN; PENTAERYTHRITOL TETRAKIS(3-(3,5-DI-TERT-BUTYL-4-HYDROXYPHENYL)PROPIONATE); CUCUMBER; SALICORNIA EUROPAEA WHOLE; RAPHANUS SATIVUS VAR. SATIVUS SEED; ALCOHOL; OCTYLDODECANOL; DIBUTYL ADIPATE; MEDIUM-CHAIN TRIGLYCERIDES; POLYESTER-8 (1400 MW, CYANODIPHENYLPROPENOYL CAPPED); LAURYL LACTATE; AMYRIS BALSAMIFERA OIL; ARABICA COFFEE OIL; BALSAM PERU OIL; DIETHYLHEXYL SYRINGYLIDENEMALONATE; BERGAMOT OIL; AVOCADO OIL; CHONDRUS CRISPUS; GRAPE SEED OIL; SANDALWOOD OIL; CITRIC ACID MONOHYDRATE; HORDEUM VULGARE WHOLE; GLYCERIN; POLYAMIDE-3 (12000 MW); ALARIA ESCULENTA

Cay Skin Isle Body Oil SPF 30

Active ingredients

Avobenzone 3%

Homosalate 10%

Octisalate 5%

Octocrylene 10%

Purpose

Sunscreen

Uses

- Helps prevent sunburn
- If used as directed with other sun protection measures (see Directions) decreases the risk of skin cancer and early skin aging caused by the sun.

Warnings

For external use only.

Do not use

on damaged or broken skin.

When using this product

keep out of eyes. Rinse with water to remove.

Stop use and consult a doctor

if skin rash occurs.

Keep out of reach of children.

If product is swallowed, get medical help or contact a Poison Control Center right away.

Flammable

Do not use near heat, flame, or while smoking.

Directions

- Adults and children over 6 months of age:
- Apply liberally 15 minutes before sun exposure.
- Reapply: at least every 2 hours; immediately after towel drying. Use a water resistant sunscreen if swimming or sweating.
- Children under 6 months of age: ask a doctor.
- Sun Protection Measures.
- Spending time in the sun increases your risk of skin cancer and early skin aging.
- To decrease this risk regularly use a sunscreen with a Broad Spectrum SPF value of 15 or higher and other sun protection measures including: limit time in the sun, especially from 10 a.m. - 2 p.m.; wear long-sleeved shirts, pants, hats and sunglasses.

Other information

Protect this product from excessive heat and direct sun.

Inactive ingredients

Alcohol, C12-15 Alkyl Benzoate, Octyldodecanol, Dibutyl Adipate, Caprylic/CapricTriglyceride, Diethylhexyl Carbonate, Diisopropyl Sebacate, Polyester-8, Lauryl Lactate, Polyamide-3, Persea Gratissima (Avocado) Oil Chondrus Crispus Extract, Alaria Esculenta Extract, Tocopheryl Acetate, Vitis Vinifera (Grape) Seed Oil, Butyrospermum Parkii (Shea) Butter, Argania Spinosa Kernel Oil, Cucumis Sativus (Cucumber) Fruit Extract Heliarrthus Annuus (Sunflower) Seed Extract, Hordeum Vulgare Extract, Salicornia Herbacea Extract, Squalane, Glycerin, Raphanus Sativus (Radish) Seed Extract, Glycine Soja (Soybean) Oil, Limnanthes Alba (Meadowfoam) Seed Oil, Amyris Balsamifera Bark Oil, Citrus Aurantium Amara (Bitter Orange) Flower Oil, Citrus Aurantium Bergamia (Bergamot) Fruit Oil, Coffea Arabica (Coffee) Seed Oil, Cupressus Sempervirens Leaf/Nut/Stem Oil, Helianthus Annuus (Sunflower) Seed Oil, Myroxylon Pereirae (Balsam Peru) Oil, Rosa Damascena Flower Oil, Santalum Album (Sandalwood) Oil, Vanilla Planifolia Fruit Extract, Diethylhexyl Syringlidenemalonate, PentaerythrityI Tetra-di-t-butyI Hydroxyhydrocinnamate, Citric Acid

Questions or comments?

cayskin.com (256) 396-8268